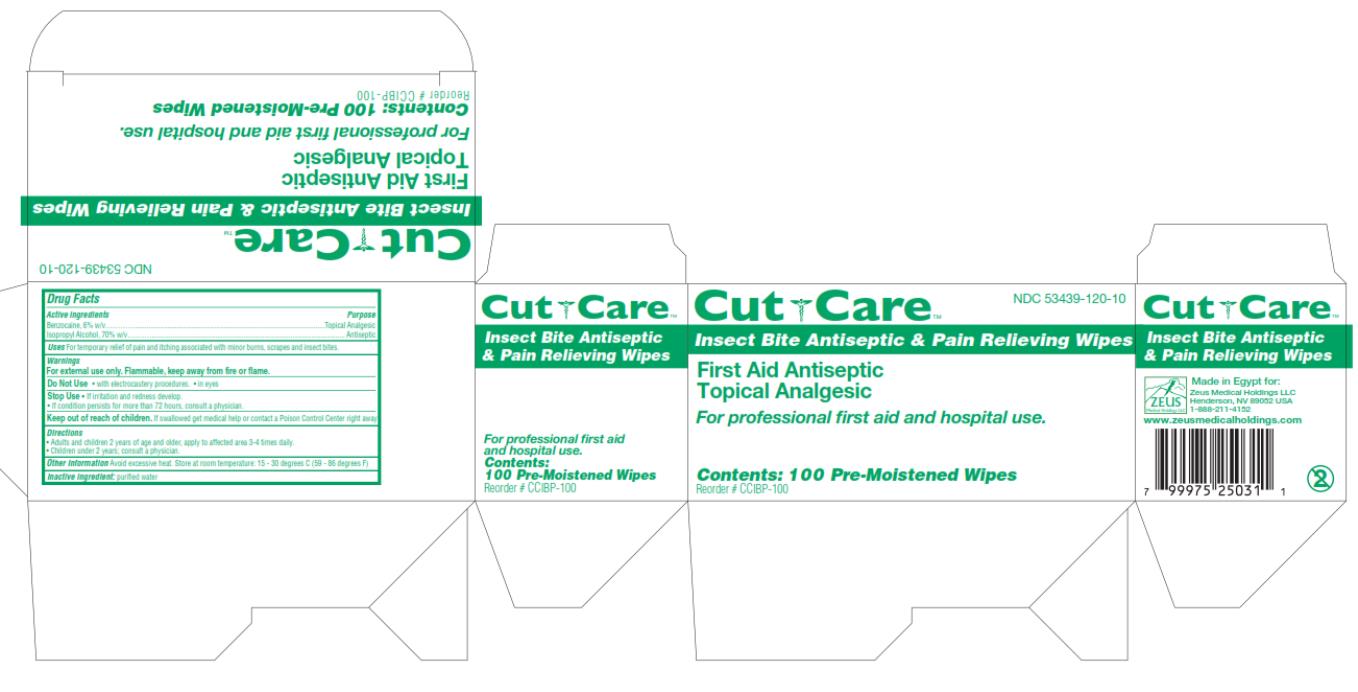 DRUG LABEL: Cut Care Insect Bite Antiseptic and Pain Relieving Wipe
NDC: 53439-120 | Form: SWAB
Manufacturer: Zeus Medical Holdings LLC
Category: otc | Type: HUMAN OTC DRUG LABEL
Date: 20130916

ACTIVE INGREDIENTS: BENZOCAINE .021 g/1 1; ISOPROPYL ALCOHOL 0.7 mL/1 1
INACTIVE INGREDIENTS: WATER

Cut Care Insect Bite Antiseptic and Pain Relieving Wipes

Active Ingredients

Benzocaine, 6% w/v

Purpose

Topical Analgesic

Active Ingredients

Isopropyl Alcohol, 70% w/v

Purpose

Antiseptic

Uses

For temporary relief of pain and itching associated with minor burns, scrapes and insect bites.

Warnings

For external use only. Flammable, keep away from fire or flame.

Do Not Use

- With electrocautery procedures.
- In eyes

Stop Use

- If irritation and redness develop.
- If condition persists for more than 72 hours, consult a physician.

Keep out of Reach of Children.

If swallowed get medical help or contact a Poison Control Center right away

Directions

- Adults and children 2 years of age and older, apply to affected area 3-4 times daily.
- Children under 2 years; consult a physician.

Other Information

Avoid excessive heat. Store at room temperature: 15 - 30 degrees C (59 - 86 degrees F)

Inactive Ingredient:

purified water

PRINCIPAL DISPLAY PANEL

NDC 53439-120-10
Cut Care
Insect Bite Antiseptic & Pain Relieving Wipes
First aid antiseptic
Topical Analgesic
Contents: 100 Pre-Moistened Wipes